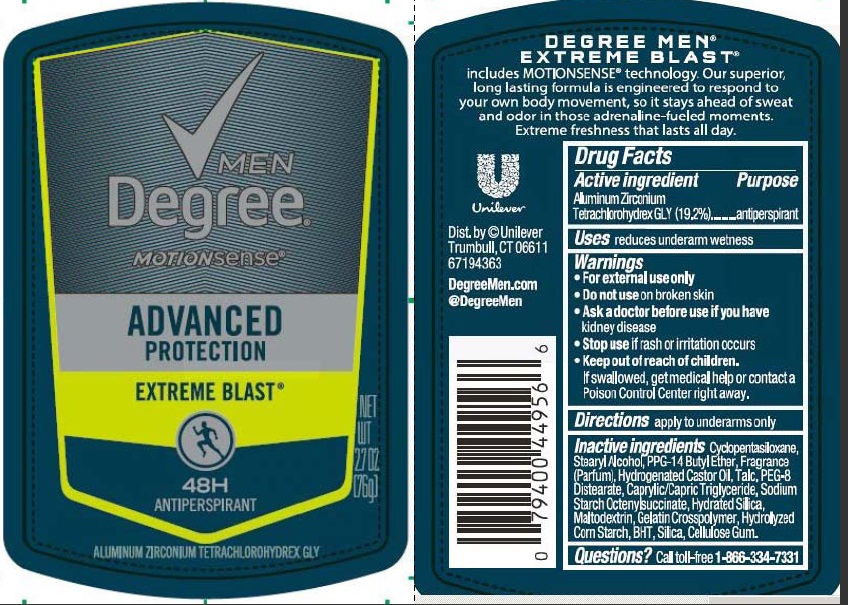 DRUG LABEL: Degree Men
NDC: 64942-1500 | Form: STICK
Manufacturer: Conopco Inc. d/b/a/ Unilever
Category: otc | Type: HUMAN OTC DRUG LABEL
Date: 20211201

ACTIVE INGREDIENTS: ALUMINUM ZIRCONIUM TETRACHLOROHYDREX GLY 19.2 g/100 g
INACTIVE INGREDIENTS: STEARYL ALCOHOL; CYCLOMETHICONE 5; PPG-14 BUTYL ETHER; HYDROGENATED CASTOR OIL; TALC; PEG-8 DISTEARATE; MEDIUM-CHAIN TRIGLYCERIDES; HYDRATED SILICA; MALTODEXTRIN; STARCH, CORN; BUTYLATED HYDROXYTOLUENE; SILICON DIOXIDE; CARBOXYMETHYLCELLULOSE SODIUM

Degree Men Motionsense Advanced Protection Extreme Blast 48H Antiperspirant - aluminum zirconium tetrachlorohydrex gly stick

Degree Men MotionSense Advanced Protection Extreme Blast 48H Antiperspirant

Drug Facts Active ingredient

Aluminum Zirconium Tetrachlorohydrex GLY (19.2 %)

Purpose

antiperspirant

Uses

reduces underarm wetness

Warnings

• For external use only.

• Do not use on broken skin.

• Ask a doctor before use if you have kidney disease.

• Stop use if rash or irritation occurs.

• Keep out of reach of children.
If swallowed, get medical help or contact a Poison Control Center right away.

Directions

apply to underarms only

Inactive ingredients

Cyclopentasiloxane, Stearyl Alcohol, PPG-14 Butyl Ether, Fragrance (Parfum), Hydrogenated Castor Oil, Talc, PEG-8 Distearate, Caprylic/Capric Triglyceride, Sodium Starch Octenylsuccinate, Hydrated Silica, Maltodextrin, Gelatin Crosspolymer, Hydrolyzed Corn Starch, BHT, Silica, Cellulose Gum

Questions?

Call toll-free 1-866-334-7331